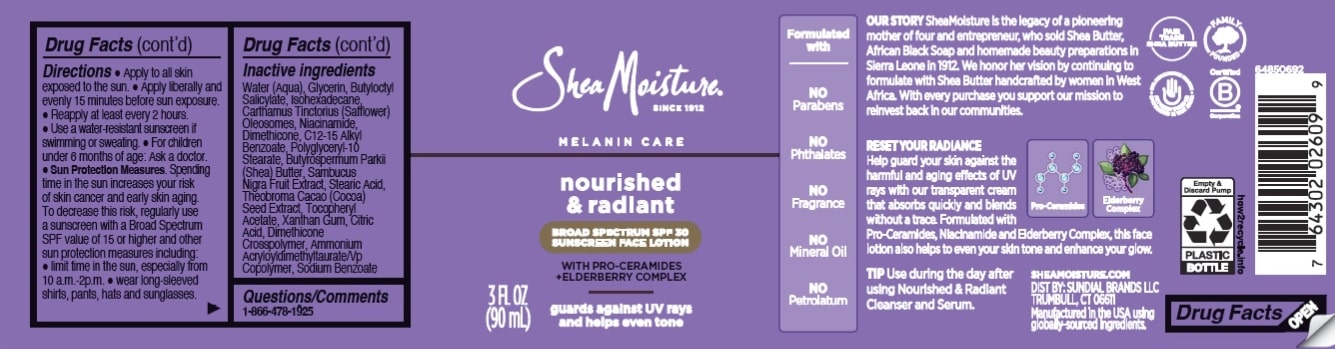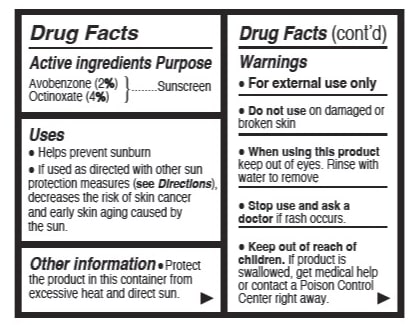 DRUG LABEL: Shea Moisture
NDC: 64942-2354 | Form: LOTION
Manufacturer: Conopco d/b/a/ Unilever
Category: otc | Type: HUMAN OTC DRUG LABEL
Date: 20250327

ACTIVE INGREDIENTS: AVOBENZONE 2 g/100 mL; OCTINOXATE 4 g/100 mL
INACTIVE INGREDIENTS: C12-15 ALKYL BENZOATE; COCOA; .ALPHA.-TOCOPHEROL ACETATE; WATER; GLYCERIN; NIACINAMIDE; BUTYLOCTYL SALICYLATE; ISOHEXADECANE; POLYGLYCERYL-10 STEARATE; BUTYROSPERMUM PARKII (SHEA) BUTTER; STEARIC ACID; DIMETHICONE CROSSPOLYMER; EUROPEAN ELDERBERRY; XANTHAN GUM; DIMETHICONE; CITRIC ACID; AMMONIUM ACRYLOYLDIMETHYLTAURATE/VP COPOLYMER; SODIUM BENZOATE; CARTHAMUS TINCTORIUS (SAFFLOWER) OLEOSOMES

Shea Moisture Nourished & Radiant Broad Spectrum SPF 30 Sunscreen Face Lotion

DESCRIPTION

Shea Moisture Nourished & Radiant Broad Spectrum SPF 30 Sunscreen Face Lotion

ACTIVE INGREDIENT

2% Avobenzone
4% Octinoxate

PURPOSE

Sunscreen

INDICATIONS AND USAGE

Helps prevent sunburn

If used as directed with other sun protection measures (see Directions), decreases the risk of skin cancer and early skin aging caused by the sun.

WARNINGS

For external use only

Do not use on damaged or broken skin

When using this product keep out of eyes. Rinse with water to remove

Stop use and ask a doctor if rash occurs.

Keep out of reach of children. If product is swallowed, get medical help or contact a Poison Control Center right away.

DOSAGE AND ADMINISTRATION

Apply to all skin exposed to the sun.

Apply liberally and evenly 15 minutes before sun exposure.

Reapply at least every 2 hours.

Use a water-resistant sunscreen if swimming or sweating.

For children under 6 months of age: Ask a doctor.

Sun Protection Measures. Spending time in the sun increases your risk of skin cancer and early skin aging. To decrease this risk, regularly use a sunscreen with a Broad Spectrum SPF value of 15 or higher and other sun protection measures including:

limit time in the sun, especially from 10 a.m.-2p.m.

wear long-sleeved shirts, pants, hats and sunglasses.

OTHER SAFETY INFORMATION

Protect the product in this container from excessive heat and direct sun.

INACTIVE INGREDIENT

Water (Aqua), Glycerin, Butyloctyl Salicylate, Isohexadecane, Carthamus Tinctorius (Safflower) Oleosomes, Niacinamide, Dimethicone, C12-15 Alkyl Benzoate, Polyglyceryl-10 Stearate, Butyrospermum Parkii (Shea) Butter, Sambucus Nigra Fruit Extract, Stearic Acid, Theobroma Cacao (Cocoa) Seed Extract, Tocopheryl Acetate, Xanthan Gum, Citric Acid, Dimethicone Crosspolymer, Ammonium Acryloyldimethyltaurate/Vp Copolymer, Sodium Benzoate

QUESTIONS

1-866-478-1925

Keep out of reach of children. If product is swallowed, get medical help or contact a Poison Control Center right away.